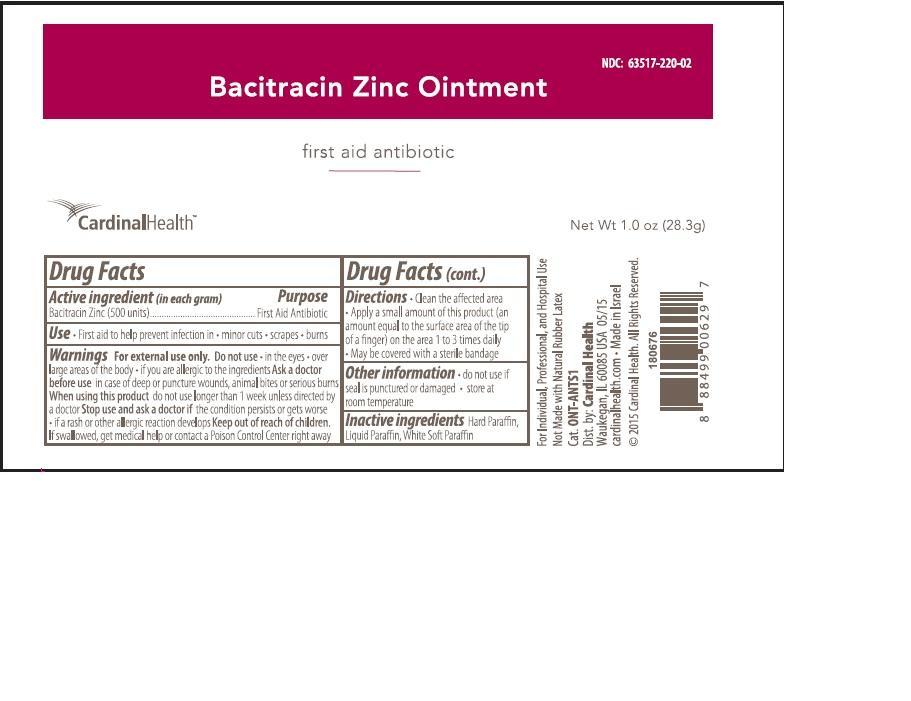 DRUG LABEL: Cardinal Health
NDC: 63517-220 | Form: OINTMENT
Manufacturer: Cardinal Health
Category: otc | Type: HUMAN OTC DRUG LABEL
Date: 20221212

ACTIVE INGREDIENTS: BACITRACIN ZINC 500 U/1 g
INACTIVE INGREDIENTS: PARAFFIN; MINERAL OIL

Drug Facts

Active ingredient (in each gram)

Bacitracin Zinc (500 units)

Purpose

First Aid Antibiotic

Uses

First aid to help prevent infection in

- Minor cuts
- Scrapes
- Burns

Warnings

For external use only.

Do not use

- in the eyes
- over large areas of the body
- if you are allergic to the ingredients

Ask a doctor before use

- in case of deep or puncture wounds, animal bites or serious burns

When using this product

do not use longer than 1 week unless directed by a doctor

Stop use and ask a doctor if

the condition persists or gets worse. If a rash or other allergenic reaction develops

Keep out of reach of children.

If swallowed, get medical help or contact a Poison Control Center right away

Directions

- Clean the affected area
- Apply a small amount of this product (an amount equal to the surface area of the tip of the finger) on the area 1 to 3 times daily
- May be covered with a sterile bandage

Other information

- do not use if seal is punctured or damaged
- store at room temperature

Inactive ingredients

Hard Paraffin, Liquid Paraffin, White Soft Paraffin

Principal Display Panel

Bacitracin Zinc Ointment

first aid antibiotic

Cardinal Health

NDC 63517-220-02

Net Wt. 1.0 oz (28.3g)